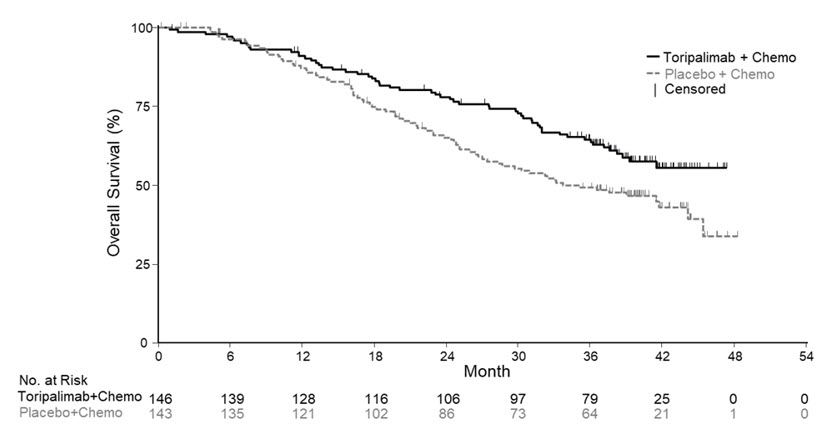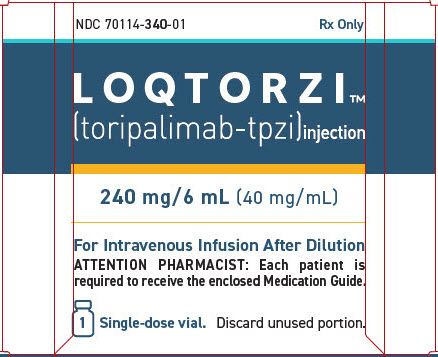 DRUG LABEL: LOQTORZI
NDC: 70114-340 | Form: INJECTION
Manufacturer: Coherus Oncology, Inc.
Category: prescription | Type: HUMAN PRESCRIPTION DRUG LABEL
Date: 20260105

ACTIVE INGREDIENTS: toripalimab 240 mg/6 mL

HIGHLIGHTS OF PRESCRIBING INFORMATION

These highlights do not include all the information needed to use LOQTORZI safely and effectively. See full prescribing information for LOQTORZI.
LOQTORZI® (toripalimab-tpzi) injection, for intravenous use
Initial U.S. Approval: 2023

RECENT MAJOR CHANGES

Warnings and Precautions (5.1) 04/2024

Dosage and Administration (2) 10/2024

1 INDICATIONS AND USAGE

LOQTORZI is a programmed death receptor-1 (PD-1)- blocking antibody indicated:

- in combination with cisplatin and gemcitabine, for first-line treatment of adults with metastatic or with recurrent locally advanced nasopharyngeal carcinoma (NPC) (1.1)
- as a single agent for the treatment of adults with recurrent unresectable or metastatic NPC with disease progression on or after a platinum-containing chemotherapy (1.2)

2 DOSAGE AND ADMINISTRATION

In combination with cisplatin and gemcitabine:

- 240 mg intravenously every three weeks (2.1)

As a single agent:

- 3 mg/kg intravenously every two weeks (2.1)

First Infusion: Infuse over 60 minutes.

Subsequent Infusions: If no infusion-related reactions occurred during the first infusion, subsequent infusions may be administered over 30 minutes.

3 DOSAGE FORMS AND STRENGTHS

Injection: 240 mg/6 mL (40 mg/mL) solution in a single-dose vial (3)

4 CONTRAINDICATIONS

None

5 WARNINGS AND PRECAUTIONS

- Immune-Mediated Adverse Reactions (5.1)
  - Immune-mediated adverse reactions, which may be severe or fatal, can occur in any organ system or tissue, including the following: immune-mediated pneumonitis, immune-mediated colitis, immune-mediated hepatitis, immune-mediated endocrinopathies, immune-mediated nephritis with renal dysfunction, immune-mediated dermatologic adverse reactions, and solid organ transplant rejection.
  - Monitor for early identification and management. Evaluate liver enzymes, creatinine, and thyroid function at baseline and periodically during treatment. (5.1)
  - Withhold or permanently discontinue based on severity and type of reaction. (5.1)
- Infusion-related reactions: Interrupt, slow the rate of infusion, or permanently discontinue LOQTORZI based on the severity of reaction. (5.2)
- Complications of allogeneic HSCT: Fatal and other serious complications can occur in patients who receive allogeneic HSCT before or after being treated with a PD-1/PD-L1 blocking antibody. (5.3)
- Embryo-fetal toxicity: Can cause fetal harm. Advise females of reproductive potential of the potential risk to a fetus and to use effective method of contraception. (5.4, 8.1, 8.3)

6 ADVERSE REACTIONS

- LOQTORZI in Combination with Cisplatin and Gemcitabine
  The most common adverse reactions (≥ 20%) are nausea, vomiting, decreased appetite, constipation, hypothyroidism, rash, pyrexia, diarrhea, peripheral neuropathy, cough, musculoskeletal pain, upper respiratory infection, insomnia, dizziness, and malaise. (6.1)
- LOQTORZI as a Single Agent
  The most common adverse reactions (≥ 20%) are fatigue, hypothyroidism and musculoskeletal pain. (6.1)

To report SUSPECTED ADVERSE REACTIONS, contact Coherus Oncology, Inc. at 1-800-483-3692 or FDA at 1-800-FDA-1088 or www.fda.gov/medwatch.

8 USE IN SPECIFIC POPULATIONS

Lactation: Advise not to breastfeed. (8.2)

FULL PRESCRIBING INFORMATION

1 INDICATIONS AND USAGE

1.1 First-line Treatment of Metastatic or Recurrent, Locally Advanced NPC with Cisplatin and Gemcitabine

LOQTORZI is indicated, in combination with cisplatin and gemcitabine, for the first-line treatment of adults with metastatic or with recurrent, locally advanced nasopharyngeal carcinoma (NPC).

1.2 Previously Treated Unresectable or Metastatic NPC

LOQTORZI is indicated, as a single agent, for the treatment of adults with recurrent unresectable or metastatic NPC with disease progression on or after a platinum-containing chemotherapy.

2 DOSAGE AND ADMINISTRATION

2.1 Recommended Dosage

The recommended dosages of LOQTORZI are provided in Table 1. Administer as recommended [see Dosage and Administration (2.3)].

Table 1: Recommended Dosage
Indication | Recommended Dosage of LOQTORZI | Duration of Treatment
First-line NPC | 240 mg every three weeks | Until disease progression, unacceptable toxicity, or up to 24 months.
Recurrent NPC | 3 mg/kg every two weeks | Until disease progression or unacceptable toxicity.

2.2 Dosage Modifications

No dose reductions of LOQTORZI are recommended. In general, withhold LOQTORZI for severe (Grade 3) immune-mediated adverse reactions. Permanently discontinue LOQTORZI for life-threatening (Grade 4) immune-mediated adverse reactions, recurrent severe (Grade 3) immune-mediated reactions that require systemic immunosuppressive treatment, or an inability to reduce prednisone to 10 mg per day or less (or equivalent) within 12 weeks of initiating steroids.

Dosage modifications for LOQTORZI for adverse reactions that require management different from these general guidelines are summarized in Table 2.

Table 2: Recommended Dosage Modifications for Adverse Reactions
Adverse Reaction | Severity [Based on National Cancer Institute (NCI) Common Terminology for Adverse Events (CTCAE) version 5.0] | Dose Modification
Immune-Related Adverse Reactions [see Warnings and Precautions (5.1)]
Pneumonitis | Grade 2 | Withhold [Resume LOQTORZI in patients with complete or partial resolution to Grade 0-1 after corticosteroid taper. Permanently discontinue if no complete or partial resolution within 12 weeks of initiating steroids or inability to reduce prednisone to 10 mg per day or less (or equivalent) within 12 weeks of initiating steroids.]
Pneumonitis | Grades 3 or 4 | Permanently discontinue
Colitis | Grade 2 or 3 | Withhold
Colitis | Grade 4 | Permanently discontinue
Hepatitis with no tumor involvement of the liver | AST/ALT increases to more than 3 and up to 8 times ULN or Total bilirubin increases to more than 1.5 and up to 3 times ULN | Withhold
Hepatitis with no tumor involvement of the liver | AST or ALT increases to more than 8 times ULN or Total bilirubin increases to more than 3 times ULN | Permanently discontinue
Hepatitis with tumor involvement of the liver [If AST and ALT are less than or equal to ULN at baseline in patients with liver involvement, withhold or permanently discontinue LOQTORZI based on recommendations for hepatitis with no liver involvement.] | Baseline AST or ALT is more than 1 and up to 3 times ULN and increases to more than 5 and up to 10 times ULN or Baseline AST or ALT is more than 3 and up to 5 times ULN and increases to more than 8 and up to 10 times ULN | Withhold
Hepatitis with tumor involvement of the liver [If AST and ALT are less than or equal to ULN at baseline in patients with liver involvement, withhold or permanently discontinue LOQTORZI based on recommendations for hepatitis with no liver involvement.] | Baseline AST or ALT is above the ULN and increases to more than 10 times ULN or Total bilirubin increases to more than 3 times ULN | Permanently discontinue
Endocrinopathies | Grades 3 or 4 | Withhold until clinically stable or permanently discontinue depending on severity
Nephritis with Renal Dysfunction | Grade 2 or 3 increased blood creatinine | Withhold
Nephritis with Renal Dysfunction | Grade 4 increased blood creatinine | Permanently discontinue
Exfoliative Dermatologic Conditions | Suspected SJS, TEN, or DRESS | Withhold
Exfoliative Dermatologic Conditions | Confirmed SJS, TEN, or DRESS | Permanently discontinue
Myocarditis | Grades 2, 3, or 4 | Permanently discontinue
Neurological toxicities | Grade 2 | Withhold
Neurological toxicities | Grade 3-4 | Permanently discontinue
Other Adverse Reactions
Infusion-related reactions [see Warnings and Precautions (5.2)] | Grade 1 or 2 | Interrupt or slow the rate of infusion
Infusion-related reactions [see Warnings and Precautions (5.2)] | Grade 3 or 4 | Stop infusion Permanently discontinue
ALT=alanine aminotransferase, AST=aspartate aminotransferase, DRESS=drug rash with eosinophilia and systemic symptoms, SJS=Stevens Johnson syndrome, TEN=toxic epidermal necrolysis, ULN=upper limit of normal

2.3 Preparation and Administration

Preparation for Intravenous Infusion

- Visually inspect the solution for particulate matter and discoloration. The solution is clear to slightly opalescent, colorless to slightly yellow. Discard the vial if visible particles are observed.
- Withdraw the required volume of LOQTORZI and inject slowly into a 100 mL or 250 mL infusion bag containing 0.9% Sodium Chloride Injection, USP. Mix diluted solution by gentle inversion. Do not shake. The final concentration of the diluted solution should be between 1 mg/mL to 3 mg/mL.
- Discard any unused portion left in the vial.

Storage of Diluted Solution for Infusion

LOQTORZI does not contain a preservative.

If the diluted solution is not administered immediately, store either:

- At room temperature, 20°C to 25°C (68°F to 77°F), for no more than 8 hours from the time of dilution to the completion of the infusion. Discard diluted solution stored at room temperature after 8 hours.
  Or
- Refrigerated at 2°C to 8°C (36°F to 46°F) for no more than 24 hours from the time of dilution to the completion of the infusion. If refrigerated, allow the diluted solution to come to room temperature prior to administration. Discard the refrigerated diluted solution after 24 hours.

Do not freeze.

Administration

- Administer diluted solution intravenously via an infusion pump using an in-line aseptic filter (0.2 or 0.22 micron).
- First Infusion: Infuse over at least 60 minutes.
- Subsequent infusions: If no infusion-related reactions occurred during the first infusion, subsequent infusions may be administered over 30 minutes [see Dose Modifications (2.2)].
- Do not co-administer other drugs through the same intravenous line.
- When administered on the same day as chemotherapy, LOQTORZI should be administered prior to chemotherapy.
- Refer to the Prescribing Information for cisplatin and gemcitabine for recommended dosing information.

3 DOSAGE FORMS AND STRENGTHS

Injection: 240 mg/6 mL (40 mg/mL) clear to slightly opalescent, colorless to slightly yellow solution in a single-dose vial.

4 CONTRAINDICATIONS

None.

5 WARNINGS AND PRECAUTIONS

5.1 Severe and Fatal Immune-Mediated Adverse Reactions

LOQTORZI is a monoclonal antibody that belongs to a class of drugs that bind to either the programmed death receptor-1 (PD-1) or PD-ligand 1 (PD-L1), blocking the PD-1/PD-L1 pathway, thereby removing inhibition of the immune response, potentially breaking peripheral tolerance and inducing immune-mediated adverse reactions. Important immune-mediated adverse reactions listed under WARNINGS AND PRECAUTIONS may not include all possible severe and fatal immune-mediated reactions.

Immune-mediated adverse reactions, which may be severe or fatal, can occur in any organ system or tissue and can affect more than one body system simultaneously. Immune-mediated adverse reactions can occur at any time after starting PD-1/PD-L1 blocking antibody. While immune-mediated adverse reactions usually manifest during treatment with PD-1/PD-L1 blocking antibodies, immune-mediated adverse reactions can also manifest after discontinuation of PD-1/PD-L1 blocking antibodies.

Early identification and management of immune-mediated adverse reactions are essential to ensure safe use of PD-1/PD-L1 blocking antibodies. Monitor closely for symptoms and signs that may be clinical manifestations of underlying immune-mediated adverse reactions. Evaluate liver enzymes, creatinine, and thyroid function at baseline and periodically during treatment. In cases of suspected immune-mediated adverse reactions, initiate appropriate workup to exclude alternative etiologies, including infection. Institute medical management promptly, including specialty consultation as appropriate.

Withhold or permanently discontinue LOQTORZI depending on severity [see Dosage and Administration (2.2)]. In general, if LOQTORZI requires interruption or discontinuation, administer systemic corticosteroid therapy (1 to 2 mg/kg/day prednisone or equivalent) until improvement to Grade 1 or less. Upon improvement to Grade 1 or less, initiate corticosteroid taper and continue to taper over at least 1 month. Consider administration of other systemic immunosuppressants in patients whose immune-mediated adverse reactions are not controlled with corticosteroid therapy.

Toxicity management guidelines for adverse reactions that do not necessarily require systemic steroids (e.g., endocrinopathies and dermatologic reactions) are discussed below.

Immune-Mediated Pneumonitis

LOQTORZI in Combination with Cisplatin and Gemcitabine

LOQTORZI in combination with cisplatin and gemcitabine can cause immune-mediated pneumonitis. In patients treated with other PD-1/PD-L1 blocking antibodies, the incidence of pneumonitis is higher in patients who have received prior thoracic radiation. Immune-mediated pneumonitis occurred in 2.1% (3/146) of patients receiving LOQTORZI, including Grade 2 (1.4%) adverse reactions. Pneumonitis resolved in 67% (2/3) of these patients.

LOQTORZI as a Single-Agent

LOQTORZI can cause immune-mediated pneumonitis. In patients treated with other PD-1/PD-L1 blocking antibodies, the incidence of pneumonitis is higher in patients who have received prior thoracic radiation. Immune-mediated pneumonitis occurred in 2.6% (22/851) of patients receiving LOQTORZI, including fatal (0.2%), Grade 3 (0.7%), and Grade 2 (1.1%) adverse reactions. Systemic corticosteroids were required in 82% (18/22) of patients with pneumonitis. Pneumonitis led to permanent discontinuation of LOQTORZI in 1.2% (10/851) of patients. Pneumonitis resolved in 23% (5/22) of these patients.

Immune-Mediated Colitis

LOQTORZI can cause immune-mediated colitis, which may present with diarrhea. Cytomegalovirus (CMV) infection/reactivation has been reported in patients with corticosteroid-refractory immune-mediated colitis. In cases of corticosteroid-refractory colitis, consider repeating infectious workup to exclude alternative etiologies.

LOQTORZI as a Single-Agent

Immune-mediated colitis occurred in 0.4% (3/851) of patients receiving LOQTORZI, including Grade 3 (0.2%) and Grade 2 (0.1%) adverse reactions. Colitis resolved in all 3 patients.

Hepatotoxicity and Immune-Mediated Hepatitis

LOQTORZI in Combination with Cisplatin and Gemcitabine

LOQTORZI in combination with cisplatin and gemcitabine can cause immune-mediated hepatitis. Immune-mediated hepatitis occurred in 0.7% (1/146) of patients receiving LOQTORZI in combination with cisplatin and gemcitabine, which was a Grade 3 (0.7%) adverse reaction. The patient with immune-mediated hepatitis required systemic corticosteroids.

LOQTORZI as a Single-Agent

LOQTORZI can cause immune-mediated hepatitis. Immune-mediated hepatitis occurred in 3.3% (28/851) of patients receiving LOQTORZI, including Grade 4 (0.8%), Grade 3 (2.1%), and Grade 2 (0.4%) adverse reactions. Hepatitis led to permanent discontinuation of LOQTORZI in 1.1% of patients and withholding of LOQTORZI in 0.8% of patients. Hepatitis resolved in 54% (15/28) of these patients.

Immune-Mediated Endocrinopathies

Adrenal Insufficiency

LOQTORZI can cause primary or secondary adrenal insufficiency. For Grade 2 or higher adrenal insufficiency, initiate symptomatic treatment, including hormone replacement as clinically indicated. Withhold or permanently discontinue LOQTORZI depending on severity [see Dosage and Administration (2.2)].

LOQTORZI as a Single-Agent

Adrenal insufficiency occurred in 0.5% (4/851) of the patients receiving LOQTORZI, including Grade 2 (0.4%) and Grade 1 (0.1%) adverse reactions. Systemic corticosteroids were required in 75% (3/4) of the patients with adrenal insufficiency. Adrenal insufficiency led to withholding of LOQTORZI in 0.1% (1/851) of patients. In the one patient in whom LOQTORZI was withheld, LOQTORZI was reinitiated after symptom improvement.

Hypophysitis

LOQTORZI can cause immune-mediated hypophysitis. Hypophysitis can present with acute symptoms associated with mass effects such as headache, photophobia, or visual field defects. Hypophysitis can cause hypopituitarism. Initiate hormone replacement as indicated. Withhold or permanently discontinue LOQTORZI depending on severity [see Dosage and Administration (2.2)].

LOQTORZI as a Single-Agent

Hypophysitis occurred in 0.4% (3/851) of patients receiving LOQTORZI, including Grade 3 (0.2%) and Grade 2 (0.1%) adverse reactions. All three patients received systemic corticosteroids. Hypophysitis led to permanent discontinuation of LOQTORZI in 0.1% (1/851) of patients and withholding of LOQTORZI in 0.1% (1/851) of patients. The one patient in whom LOQTORZI was withheld reinitiated LOQTORZI.

Thyroid Disorders

LOQTORZI can cause immune-mediated thyroid disorders. Thyroiditis can present with or without endocrinopathy. Hypothyroidism can follow hyperthyroidism. Initiate hormone replacement for hypothyroidism or institute medical management of hyperthyroidism as clinically indicated. Withhold or permanently discontinue LOQTORZI depending on severity [see Dosage and Administration (2.2)].

LOQTORZI in Combination with Cisplatin and Gemcitabine

Thyroiditis occurred in 2.1% (3/146) of patients receiving LOQTORZI in combination with cisplatin and gemcitabine, including Grade 2 (1.4%). Three patients required thyroid hormone replacement therapy. Thyroiditis resolved in one of the 3 patients.

Hyperthyroidism occurred in 1.4% (2/146) of patients receiving LOQTORZI in combination with cisplatin and gemcitabine. Hyperthyroidism resolved in these 2 patients.

Hypothyroidism occurred in 30% (44/146) of patients receiving LOQTORZI in combination with cisplatin and gemcitabine, including Grade 2 (24%) and Grade 1 (6%). Eighty percent of the 44 patients required thyroid hormone replacement therapy. LOQTORZI was withheld in 2.1% (3/146) of the patients. Of the 3 patients in whom LOQTORZI was withheld, 2 patients reinitiated LOQTORZI.

LOQTORZI as a Single-Agent

Thyroiditis occurred in 0.6% (5/851) of patients receiving LOQTORZI, including Grade 2 (0.1%). Two of these 5 patients received systemic corticosteroids and 2 required thyroid hormone replacement therapy. Thyroiditis resolved in 2 of the 5 patients.

Hyperthyroidism occurred in 7% (55/851) of patients receiving LOQTORZI, including Grade 2 (1.9%). Hyperthyroidism resolved in 85% (47/55) of the patients.

Hypothyroidism occurred in 15% (128/851) of patients receiving LOQTORZI, including Grade 2 (8%). Sixty three percent of the 128 patients required thyroid hormone replacement therapy. LOQTORZI was withheld in 0.5% of patients. Of the 4 patients in whom LOQTORZI was withheld, 3 patients reinitiated LOQTORZI.

Type 1 Diabetes Mellitus, which can present with Diabetic Ketoacidosis

Monitor patients for hyperglycemia or other signs and symptoms of diabetes. Initiate treatment with insulin as clinically indicated. Withhold or permanently discontinue LOQTORZI depending on severity [see Dosage and Administration (2.2)].

LOQTORZI as a Single-Agent

Diabetes mellitus occurred in 0.9% (8/851) of patients receiving LOQTORZI, including Grade 4 (0.1%), Grade 3 (0.7%), and Grade 2 (0.1%). Diabetes mellitus led to permanent discontinuation in 0.4% of patients. Six of the 8 (75%) patients with diabetes mellitus required long-term insulin therapy.

Immune-Mediated Nephritis with Renal Dysfunction

LOQTORZI in Combination with Cisplatin and Gemcitabine

LOQTORZI in combination with cisplatin and gemcitabine can cause immune-mediated nephritis. Immune-mediated nephritis occurred in 0.7% (1/146) of patients receiving LOQTORZI. The one patient with immune-mediated nephritis (Grade 4) required systemic corticosteroids and nephritis led to discontinuation of LOQTORZI. Nephritis resolved in this patient.

LOQTORZI as a Single-Agent

LOQTORZI can cause immune-mediated nephritis. Immune-mediated nephritis occurred in 0.5% (4/851) of patients receiving LOQTORZI, including Grade 3 (0.5%) adverse reactions. Nephritis resolved in 75% (3/4) of these patients.

Immune-Mediated Dermatologic Adverse Reactions

LOQTORZI can cause immune-mediated rash or dermatitis. Exfoliative dermatitis, including Stevens-Johnson Syndrome (SJS), drug rash with eosinophilia and systemic symptoms (DRESS), and toxic epidermal necrolysis (TEN), has occurred with PD-1/PD-L1 blocking antibodies. Topical emollients and/or topical corticosteroids may be adequate to treat mild to moderate non-exfoliative rashes. Withhold or permanently discontinue LOQTORZI depending on severity [see Dosage and Administration (2.2)].

LOQTORZI in Combination with Cisplatin and Gemcitabine

Immune-mediated dermatologic adverse reactions occurred in 8% (12/146) of patients receiving LOQTORZI, including Grade 3 (3.4%) and Grade 2 (1.4%) adverse reactions. Systemic corticosteroids were required in 25% (3/12) of the patients with immune-mediated dermatologic adverse reactions. Immune-mediated dermatologic adverse reactions led to permanent discontinuation of LOQTORZI in 2.1% (3) of patients. Immune-mediated dermatologic adverse reactions resolved in 92% (11/12) of these patients.

LOQTORZI as a Single-Agent

Immune-mediated dermatologic adverse reactions occurred in 4% (34/851) of patients receiving LOQTORZI, including Grade 3 (0.4%) and Grade 2 (1.4%) adverse reactions. Immune-mediated dermatologic adverse reactions led to withholding of LOQTORZI in 0.4% (3) of the patients. Systemic corticosteroids were required in 12% (4/34) of the patients with immune-mediated dermatologic adverse reactions. Immune-mediated dermatologic adverse reactions resolved in 71% (24/34) of these patients.

Other Immune-Mediated Adverse Reactions

The following clinically significant immune-mediated adverse reactions occurred at an incidence of <1% (unless otherwise noted) in patients who received LOQTORZI or were reported with the use of other PD1/PD-L1 blocking antibodies. Severe or fatal cases have been reported for some of these adverse reactions.

Cardiac/Vascular: Myocarditis, pericarditis, vasculitis, pericardial effusion

Nervous System: Meningitis, encephalitis, myelitis and demyelination, myasthenic syndrome/myasthenia gravis (including exacerbation), Guillain-Barré syndrome, nerve paresis, autoimmune neuropathy

Ocular: Uveitis, iritis and other ocular inflammatory toxicities can occur. Some cases can be associated with retinal detachment. Various grades of visual impairment, including blindness, can occur. If uveitis occurs in combination with other immune-mediated adverse reactions, consider a Vogt-Koyanagi-Harada-like syndrome, as this may require treatment with systemic steroids to reduce the risk of permanent vision loss.

Gastrointestinal: Pancreatitis, to include increases in serum amylase and lipase levels, gastritis, duodenitis

Musculoskeletal and Connective Tissue: Myositis/polymyositis, rhabdomyolysis (and associated sequelae, including renal failure), arthritis, polymyalgia rheumatica, dermatomyositis

Endocrine: Hypoparathyroidism

Hematologic/Immune: Hemolytic anemia, aplastic anemia, hemophagocytic lymphohistiocytosis, systemic inflammatory response syndrome, histiocytic necrotizing lymphadenitis (Kikuchi lymphadenitis), sarcoidosis, immune thrombocytopenic purpura, solid organ transplant rejection, other transplant (including corneal graft) rejection.

5.2 Infusion-Related Reactions

LOQTORZI can cause severe or life-threatening infusion-related reactions including hypersensitivity and anaphylaxis.

LOQTORZI in Combination with Cisplatin and Gemcitabine

Infusion-related reactions have been reported in 4.1% of patients receiving LOQTORZI in combination with cisplatin and gemcitabine, including Grade 2 (0.7%) reactions.

LOQTORZI as a Single-Agent

Infusion-related reactions occurred in 2% of 851 patients receiving LOQTORZI as single agent, including Grade 3 (0.1%) and Grade 2 (0.6%). LOQTORZI was withheld for one Grade 3 infusion related reaction.

Monitor patients for signs and symptoms of infusion-related reactions including rigors, chills, wheezing, pruritus, flushing, rash, hypotension, hypoxemia, and fever. Interrupt or slow the rate of infusion for mild (Grade 1) or moderate (Grade 2) infusion-related reactions. For severe (Grade 3) or life-threatening (Grade 4) infusion-related reactions, stop infusion and permanently discontinue LOQTORZI [see Dosage and Administration (2.2)].

5.3 Complications of Allogeneic HSCT

Fatal and other serious complications can occur in patients who receive allogeneic hematopoietic stem cell transplantation (HSCT) before or after being treated with a PD-1/PD-L1 blocking antibody. Transplant-related complications include hyperacute graft-versus-host-disease (GVHD), acute GVHD, chronic GVHD, hepatic veno-occlusive disease (VOD) after reduced intensity conditioning, and steroid-requiring febrile syndrome (without an identified infectious cause). These complications may occur despite intervening therapy between PD-1/PD-L1 blockade and allogeneic HSCT.

Follow patients closely for evidence of transplant-related complications and intervene promptly. Consider the benefit versus risks of treatment with a PD-1/PD-L1 blocking antibody prior to or after an allogeneic HSCT.

5.4 Embryo-Fetal Toxicity

Based on its mechanism of action, LOQTORZI can cause fetal harm when administered to a pregnant woman. Animal studies have demonstrated that inhibition of the PD-1/PD-L1 pathway can lead to increased risk of immune-mediated rejection of the developing fetus resulting in fetal death. Advise women of the potential risk to a fetus. Advise females of reproductive potential to use effective contraception during treatment with LOQTORZI and for 4 months after the last dose [see Use in Specific Populations (8.1, 8.3)].

6 ADVERSE REACTIONS

The following clinically significant adverse reactions are described elsewhere in the labeling:

- Severe and fatal immune-mediated adverse reactions [see Warnings and Precautions (5.1)]
- Infusion-related reactions [see Warnings and Precautions (5.2)]
- Complications of Allogeneic HSCT [see Warnings and Precautions (5.3)]

6.1 Clinical Trials Experience

Because clinical trials are conducted under widely varying conditions, adverse reaction rates observed in the clinical trials of a drug cannot be directly compared to rates in the clinical trials of another drug and may not reflect the rates observed in practice.

The data described in the WARNINGS AND PRECAUTIONS section reflect exposure to LOQTORZI at a dose of 240 mg every 3 weeks in combination with up to 6 cycles of cisplatin and gemcitabine, followed by LOQTORZI 240 mg IV every 3 weeks, in 146 patients with NPC enrolled in a randomized, double-blind, placebo-controlled trial (JUPITER-02). Among the 146 patients, 73% were exposed to LOQTORZI for 6 months or more and 54% were exposed for 12 months or more. The most common adverse reactions (≥ 20%) were: nausea (71%), vomiting (68%), decreased appetite (55%), constipation (39%), hypothyroidism (38%), rash (36%), pyrexia (32%), diarrhea (31%), peripheral neuropathy (30%), cough (26%), musculoskeletal pain (25%), upper respiratory infection (23%), insomnia (23%), dizziness (21%), and malaise (21%). The most common Grade 3 or 4 laboratory abnormalities (≥2%) were: decreased neutrophils (58%), decreased lymphocytes (57%), decreased hemoglobin (50%) decreased platelets (33%), decreased potassium (10%), decreased sodium (9%), increased alanine aminotransferase (6%) increased or decreased magnesium (4.2% each), decreased calcium (3.5%), increased aspartate aminotransferase (2.7%), and bilirubin increased (2.1%).

The data described in the WARNINGS AND PRECAUTIONS section also reflects exposure to LOQTORZI as a single agent at a dose of 3 mg/kg IV every 2 weeks in 851 patients enrolled in 12 trials: one randomized, active-controlled trial and 11 open-label, non-randomized trials. The tumor types included nasopharyngeal carcinoma (n=193) or other types of tumors (n=658). Among the 851 patients treated with LOQTORZI as a single agent, 35% were exposed for 6 months or more and 20% were exposed for 12 months or more. In this pooled safety population, the most common (≥20%) adverse reactions were: fatigue (22%), hypothyroidism (20%), and musculoskeletal pain (20%). The most common Grade 3 or 4 laboratory abnormalities (≥2%), were decreased sodium (9%), decreased lymphocytes (8%), decreased hemoglobin (7%), decreased fibrinogen (4.5%), increased lipase (4.0%), increased amylase (2.9%), decreased phosphate (2.8%), increased aspartate aminotransferase (2.6%), increased glucose (2.5%), and increased triglycerides (2.1%).

First-line Treatment of Metastatic or Recurrent, Locally Advanced Nasopharyngeal Carcinoma (NPC)

The safety of LOQTORZI in combination with cisplatin and gemcitabine was evaluated in JUPITER-02 [see Clinical Studies (14)]. Key eligibility criteria were recurrent locally advanced or metastatic nasopharyngeal carcinoma (NPC) not previously treated with systemic chemotherapy for recurrent or metastatic disease. Patients with recurrent NPC after treatment with curative intent were required to have an interval of at least 6 months between the last dose of radiotherapy or chemotherapy and recurrence. Patients received LOQTORZI 240 mg (n=146) or placebo intravenously (IV) every 3 weeks (n=143), in combination with cisplatin 80 mg/m^2 IV every 3 weeks and gemcitabine 1000 mg/m^2 IV days 1 and 8 for up to 6 cycles followed by LOQTORZI 240 mg or placebo IV every 3 weeks until disease progression, unacceptable toxicity, or completion of 2 years of treatment. Among patients who received LOQTORZI, 73% were exposed for 6 months or longer and 54% were exposed for greater than one year.

The median age of patients who received LOQTORZI was 48 years (range: 19 to 72), 83% male, 100% Asian, 60% had recurrent disease, and 40% presented with metastatic disease. Eastern Cooperative Oncology Group (ECOG) Performance Status (PS) was 0 (57%) or 1 (43%). Approximately 59% of patients had received at least one prior systemic therapy for locally advanced disease and 60% had received prior radiation therapy.

Serious adverse reactions occurred in 43% of patients receiving LOQTORZI in combination with cisplatin and gemcitabine. Serious adverse drug reactions in ≥ 2% were thrombocytopenia (14%), neutrophil count decreased (10%), pneumonia (10%), anemia (9%), abnormal hepatic function (2.7%), and rash (2.1%). Of the patients who received LOQTORZI in combination with cisplatin and gemcitabine, there were three fatal adverse reactions (2.1%) one due to epistaxis; one due to intracranial hemorrhage associated with immune-related thrombocytopenia and coagulopathy; and one due to pneumonia.

Permanent discontinuation of LOQTORZI, when given in combination with cisplatin and gemcitabine, due to an adverse reaction occurred in 12% of patients. Adverse reactions resulting in permanent discontinuation of LOQTORZI in ≥1% were pneumonia (2.1%), pulmonary tuberculosis (1.4%), rash (1.4%), and vomiting (1.4%).

Dosage interruptions of LOQTORZI due to an adverse reaction occurred in 50% of patients. Adverse reactions which required dosage interruption in ≥2% were anemia (17%), decreased neutrophils (12%), thrombocytopenia (12%), acute kidney injury (4.1%), pneumonia (6%), fatigue (2.7%), upper respiratory infection (2.7%), and hypothyroidism (2.1%).

Table 3 summarizes the adverse reactions in JUPITER-02.

Table 3: Adverse Reactions (≥ 10%) in Patients with Recurrent, Locally Advanced or Metastatic NPC Who Received LOQTORZI in Combination with Cisplatin and Gemcitabine in JUPITER-02
Adverse Reaction [NCI CTCAE v5.0.] | LOQTORZI Cisplatin/Gemcitabine N = 146 |  | Placebo Cisplatin/Gemcitabine N = 143
Adverse Reaction [NCI CTCAE v5.0.] | All Grades (%) | Grade 3 or 4 (%) | All Grades (%) | Grade 3 or 4 (%)
Gastrointestinal Disorders
Nausea | 71 | 1.4 | 84 | 2.8
Vomiting | 68 | 2.1 | 66 | 2.1
Constipation | 39 | 0 | 46 | 0
Diarrhea | 31 | 1.4 | 23 | 0
Stomatitis [Includes mouth ulceration, stomatitis, and radiation stomatitis.] | 12 | 0 | 8 | 0.7
Metabolism and Nutrition Disorders
Decreased appetite | 55 | 0.7 | 63 | 0
Endocrine Disorders
Hypothyroidism [Includes hypothyroidism, tri-iodothyronine decreased, tri-iodothyronine free decreased, and thyroiditis.] | 38 | 0.7 | 17 | 0
Skin Disorders
Rash [Includes acneiform dermatitis, allergic dermatitis, catheter-site rash, dermatitis, drug eruption, eczema, erythema, macule, maculopapular rash, palmar-plantar erythrodysesthesia syndrome, papule, pruritic rash, rash, and urticaria.] | 36 | 3.4 | 28 | 2.8
Pruritus | 17 | 0 | 8 | 0
General Disorders
Pyrexia | 32 | 1.4 | 24 | 0.7
Malaise | 21 | 0.7 | 20 | 0
Fatigue [Includes asthenia and fatigue.] | 19 | 0.7 | 22 | 2.1
Nervous System Disorders
Peripheral neuropathy [Includes hypoesthesia, neuralgia, neuropathy peripheral, paresthesia, peripheral sensory neuropathy.] | 30 | 0 | 31 | 0.7
Dizziness | 21 | 0 | 22 | 0.7
Headache | 18 | 0 | 23 | 0.7
Respiratory, Thoracic and Mediastinal Disorders
Cough [Includes cough and productive cough.] | 26 | 0 | 27 | 0
Musculoskeletal Disorders
Musculoskeletal pain [Includes back pain, bone pain, musculoskeletal chest pain, musculoskeletal pain, myalgia, neck pain, pain in extremity, pain in jaw.] | 25 | 0 | 25 | 0.7
Infections
Upper respiratory infection [Includes acute sinusitis, bronchitis, laryngitis, nasopharyngitis, pharyngitis, respiratory tract infection, rhinitis, sinusitis, and upper respiratory tract infection.] | 23 | 3.4 | 13 | 2.8
Pneumonia [Includes aspiration pneumonia and pneumonia] | 18 | 11 | 7 | 3.5
Psychiatric Disorders
Insomnia | 23 | 0 | 17 | 0
Vascular Disorders
Epistaxis | 10 | 1.3 | 13 | 2.8
Hypertension [Includes blood pressure increased, blood pressure systolic increased, hypertension, and hypertensive crisis.] | 10 | 6 | 6 | 4.2

Table 4 summarizes the laboratory abnormalities in JUPITER-02.

Table 4: Select Laboratory Abnormalities (≥20%) That Worsened from Baseline in Patients with Recurrent, Locally Advanced or Metastatic NPC Who Received LOQTORZI in Combination with Cisplatin and Gemcitabine in JUPITER-02
Laboratory Abnormalities [Each test incidence is based on the number of patients who had both baseline and at least one on-study laboratory measurement available: LOQTORZI/chemotherapy (range: 139 to 146 patients) and placebo/chemotherapy (range: 136 to 143 patients).] | LOQTORZI Cisplatin/Gemcitabine |  | Placebo Cisplatin/Gemcitabine
Laboratory Abnormalities [Each test incidence is based on the number of patients who had both baseline and at least one on-study laboratory measurement available: LOQTORZI/chemotherapy (range: 139 to 146 patients) and placebo/chemotherapy (range: 136 to 143 patients).] | All Grades [Graded per NCI CTCAE v5.0; AKP=alkaline phosphatase. ALT=alanine aminotransferase. AST=aspartate aminotransferase.] (%) | Grade 3 or 4 (%) | All Grades (%) | Grades 3 or 4 (%)
Hematology
Decreased hemoglobin | 94 | 50 | 97 | 38
Decreased neutrophils | 91 | 58 | 95 | 63
Decreased lymphocytes | 88 | 57 | 88 | 49
Decreased platelets | 71 | 33 | 66 | 31
Chemistry
Decreased magnesium | 78 | 4.2 | 77 | 8
Decreased sodium | 63 | 9 | 62 | 6
Increased alanine aminotransferase | 58 | 6 | 50 | 3.5
Increased aspartate aminotransferase | 58 | 2.7 | 53 | 4.9
Decreased albumin | 49 | 0 | 48 | 0
Decreased calcium | 45 | 3.5 | 46 | 4.2
Increased lactate dehydrogenase | 42 | 0 | 35 | 0
Increased calcium | 39 | 0 | 35 | 0.7
Decreased potassium | 40 | 10 | 39 | 8
Increased creatinine | 39 | 0.7 | 41 | 0
Increased alkaline phosphatase | 27 | 0 | 27 | 0
Decreased glucose | 23 | 1.4 | 16 | 0

Previously Treated, Unresectable or Metastatic Nasopharyngeal Carcinoma (NPC)

The safety of LOQTORZI was evaluated in POLARIS-02. Eligible patients had previously treated unresectable or metastatic NPC. Patients received LOQTORZI 3 mg/kg every 2 weeks as an intravenous infusion until disease progression or unacceptable toxicity. Among patients who received LOQTORZI, 33% were exposed for 6 months or longer and 21% were exposed for greater than one year.

The median age of patients who received LOQTORZI was 46 years (range: 22 to 71), 83% male, 100% Asian, Eastern Cooperative Oncology Group (ECOG) Performance Status (PS) of 0 (35%) or 1 (65%) and median weight 59 kg (range: 32 to 101 kg).

Serious adverse reactions occurred in 24% of patients who received LOQTORZI. Serious adverse drug reactions in (≥2%) were pneumonia (4.7%), abnormal hepatic function (2.6%), and hyperbilirubinemia (2.1%). Fatal adverse reactions occurred in 3.7% of patients who received LOQTORZI, including death not otherwise specified (1.6%), tumor hemorrhage (0.5%), hepatic failure and thrombocytopenia (0.5%), hyponatremia (0.5%), and sudden death (0.5%).

Permanent discontinuation of LOQTORZI due to an adverse reaction occurred in 9% of patients. Adverse reaction resulting in permanent discontinuation of LOQTORZI in ≥1% included pneumonia (1.1%), abnormal hepatic function (1.1%), and hyperbilirubinemia (1.1%).

Dosage interruptions due to an adverse reaction occurred in 23% of patients. Adverse reactions which required dosage interruption in ≥1% were pneumonia (2.1%), thrombocytopenia (2.1%), fatigue (1.6%), hyperbilirubinemia (1.6%), anemia (1.1%), decreased appetite (1.1%), abnormal hepatic function (1.1%), hypothyroidism (1.1%), and pneumonitis (1.1%).

Table 5 summarizes the adverse reactions in POLARIS-02.

Table 5: Adverse Reactions (≥10%) in Patients with Previously Treated, Unresectable or Metastatic NPC Who Received LOQTORZI in POLARIS-02
Adverse Reaction [Toxicity was graded per National Cancer Institute Common Terminology Criteria for Adverse Events (NCI CTCAE) v4.03.] | LOQTORZI N=190
 | All Grades (%) | Grade 3 or 4 (%)
Endocrine Disorders
Hypothyroidism [Includes hypothyroidism, thyroiditis, tri-iodothyronine decreased, and tri-iodothyronine free decreased] | 27 | 0
General Disorders
Fatigue [Includes fatigue and asthenia] | 22 | 2.6
Pyrexia | 16 | 0
Respiratory Disorders
Cough [Includes cough and productive cough.] | 20 | 0
Musculoskeletal Disorders
Musculoskeletal Pain [Includes musculoskeletal pain and myalgia.] | 18 | 1.1
Metabolism and Nutrition
Decreased Appetite | 13 | 1.1
Gastrointestinal Disorders
Constipation | 11 | 0
Skin and Subcutaneous Disorders
Pruritus | 11 | 0
Rash [Includes dermatitis allergic, eczema, and rash.] | 11 | 0
Investigations
Weight Decreased | 11 | 0

Table 6 summarizes the laboratory abnormalities in POLARIS-02.

Table 6: Select Laboratory Abnormalities (≥20%) That Worsened from Baseline in Patients with Previously Treated, Unresectable or Metastatic NPC Who Received LOQTORZI in POLARIS-02
 | LOQTORZI
 | All Grades (%) [Toxicity graded per NCI CTCAE v4.03. The denominator used to calculate the rate varied from 141 to 186 based on the number of patients with a baseline value and at least one post-treatment value.] | Grade 3 or 4 (%)
Chemistry
Decreased albumin | 38 | 0.5
Decreased sodium | 35 | 11
Decreased phosphate | 32 | 3.2
Increased aspartate aminotransferase | 30 | 3.8
Decreased calcium | 29 | 0.5
Increased alkaline phosphatase | 28 | 2.2
Increased triglyceride | 26 | 1.1
Increased glucose | 24 | 1.1
Increased alanine aminotransferase | 23 | 1.6
Hematology
Decreased lymphocytes | 52 | 9
Decreased hemoglobin | 43 | 6

8 USE IN SPECIFIC POPULATIONS

8.1 Pregnancy

Risk Summary

Based on its mechanism of action, LOQTORZI can cause fetal harm when administered to a pregnant woman [see Clinical Pharmacology (12.1)]. There are no available data on the use of LOQTORZI in pregnant women. Animal studies have demonstrated that inhibition of the PD-1/PD-L1 pathway can lead to increased risk of immune-mediated rejection of the developing fetus and result in fetal death (see Data). Human IgG4 immunoglobulins (IgG4) are known to cross the placenta; therefore, LOQTORZI can potentially be transmitted from the mother to the developing fetus. Advise women of the potential risk to a fetus.

In the U.S. general population, the estimated background risk of major birth defects and miscarriage in clinically recognized pregnancies is 2% to 4% and 15% to 20%, respectively.

Data

Animal Data

Animal reproduction studies have not been conducted with LOQTORZI to evaluate its effect on reproduction and fetal development. A central function of the PD-1/PD-L1 pathway is to preserve pregnancy by maintaining maternal immune tolerance to the fetus. In murine models of pregnancy, blockade of PD-L1 signaling has been shown to disrupt tolerance to the fetus and to result in an increase in fetal loss; therefore, potential risks of administering LOQTORZI during pregnancy could include increased rates of abortion or stillbirth. As reported in the literature, there were no malformations related to the blockade of PD-1/PD-L1 signaling in the offspring of these animals; however, immune-mediated disorders occurred in PD-1 and PD-L1 knockout mice. Based on its mechanism of action, fetal exposure to toripalimab-tpzi may increase the risk of developing immune-mediated disorders or altering the normal immune response.

8.2 Lactation

Risk Summary

There are no data on the presence of toripalimab-tpzi in human milk or its effects on the breastfed child or on milk production. Maternal IgG is known to be present in human milk. The effects of local gastrointestinal exposure and limited systemic exposure in the breastfed child to toripalimab-tpzi are unknown. Because of the potential for serious adverse reactions in breastfed children, advise lactating women not to breastfeed during treatment with LOQTORZI and for 4 months after the last dose.

8.3 Females and Males of Reproductive Potential

LOQTORZI can cause fetal harm when administered to a pregnant woman [see Use in Specific Populations (8.1)].

Pregnancy Testing

Verify the pregnancy status of females of reproductive potential prior to initiating LOQTORZI [see Use in Specific Populations (8.1)].

Contraception

Females

Advise females of reproductive potential to use effective contraception during treatment with LOQTORZI and for 4 months after the last dose.

8.4 Pediatric Use

The safety and effectiveness of LOQTORZI have not been established in pediatric patients [see Indications and Usage (1)].

8.5 Geriatric Use

Of the 146 patients with NPC who were treated with LOQTORZI in combination with cisplatin and gemcitabine 7 (4.8%) were 65 years or older; there were no patients 75 years and older. Clinical studies of LOQTORZI in combination with cisplatin and gemcitabine did not include a sufficient number of patients aged 65 years and over with NPC to determine whether they respond differently from younger patients.

Of the 851 patients with tumor types including nasopharyngeal carcinoma or other types of tumors from the safety pool treated with LOQTORZI as a single agent, 171 (20%) patients were 65 years or older and 13 (1.5%) patients were 75 years and older. No overall differences in safety were observed between elderly patients and younger patients [see Adverse Reactions (6.1)].

Of the 190 patients with NPC treated with LOQTORZI as single agent, 10 (5%) patients were 65 years or older; there were no patients 75 years and older. Clinical studies of LOQTORZI did not include sufficient numbers of patients aged 65 years and over with NPC to determine whether they respond differently from younger patients.

11 DESCRIPTION

Toripalimab-tpzi is a programmed death receptor-1 (PD-1) blocking antibody. Toripalimab-tpzi is a humanized immunoglobulin G4 (IgG4) kappa immunoglobulin that has a predicted molecular weight of approximately 150 kDa. It is expressed in a recombinant Chinese Hamster Ovary (CHO) mammalian cell expression system.

LOQTORZI (toripalimab-tpzi) injection is a sterile, preservative-free, clear to slightly opalescent, colorless to slightly yellow solution for intravenous use supplied in a single-dose vial. Each vial contains 240 mg of LOQTORZI in 6 mL of solution. Each mL of solution contains 40 mg toripalimab-tpzi, citric acid monohydrate (0.51 mg), mannitol (25 mg), polysorbate 80 (0.20 mg), sodium chloride (2.92 mg), sodium citrate (4.65 mg), and Water for Injection, USP, at pH 6.0.

12 CLINICAL PHARMACOLOGY

12.1 Mechanism of Action

Binding of the PD-1 ligands, PD-L1 and PD-L2, to the PD-1 receptor found on T cells, inhibits T cell proliferation and cytokine production. Upregulation of PD-1 ligands occurs in some tumors and signaling through this pathway can contribute to inhibition of active T-cell immune surveillance of tumors. Toripalimab-tpzi is a humanized IgG4 monoclonal antibody that binds to the PD-1 receptor and blocks its interaction with PD-L1 and PD-L2, releasing PD-1 pathway-mediated inhibition of the immune response, including the anti-tumor immune response. In syngeneic mouse tumor models, blocking PD-1 activity resulted in decreased tumor growth.

12.2 Pharmacodynamics

The toripalimab-tpzi exposure-response relationships and time course of pharmacodynamic response are not fully characterized.

12.3 Pharmacokinetics

Toripalimab-tpzi pharmacokinetic parameters are presented as geometric mean (coefficient of variation [CV]%) unless otherwise noted. Toripalimab-tpzi concentrations increased in non-linearly over the dose range of 0.3 to 10 mg/kg every two weeks (0.1 to 3.3 times the approved recommended 3 mg/kg dosage in a 64 kg patient). Steady state was reached by Week 7. The mean accumulation ratio was approximately 1.4 for maximum concentration (Cmax) and 1.9 for area under the serum concentration curve (AUC) following multiple doses at the approved recommended dosages of 240 mg Q3W in combination with cisplatin and gemcitabine and 3 mg/kg Q2W as monotherapy.

Distribution

The mean volume of distribution at steady state (Vss) of toripalimab-tpzi was 3.7 L (27%).

Elimination

The mean clearance (CL) was 14.9 mL/h (31%) after the first dose and 9.5 mL/h (36%) at steady state. The mean terminal half-life (t1/2) (± standard deviation) was 10 ± 1.5 days after the first dose and 18 ± 9.4 days at steady state.

Metabolism

Toripalimab-tpzi is expected to be metabolized into small peptides by catabolic pathways.

Specific Populations

No clinically significant differences in the pharmacokinetics were observed based on age (21 to 85 years), body weight (32 to 164 kg), sex, race (White and Asian), concomitant chemotherapy, mild renal impairment (creatinine clearance [CLcr] 60 to 89 mL/min), mild hepatic impairment (total bilirubin > 1 to 1.5 times ULN with any AST or total bilirubin ≤ ULN with AST > ULN), tumor burden and primary cancer.

The effect of moderate (total bilirubin >1.5 to 3 times ULN and any AST) or severe (total bilirubin > 3 times ULN and any AST) hepatic impairment or of moderate (CLcr 30 to 59 mL/min) or severe (CLcr 15 to 29 mL/min) renal impairment on the pharmacokinetics of toripalimab-tpzi has not been studied.

12.6 Immunogenicity

The observed incidence of anti-drug antibodies (ADA) is highly dependent on the sensitivity and specificity of the assay. Differences in assay methods preclude meaningful comparisons of the incidence of ADA in the studies described below with the incidence of ADA in other studies, including those of LOQTORZI or of other toripalimab products.

Of the 146 evaluable patients in JUPITER-02 with nasopharyngeal cancer who received LOQTORZI 240 mg every 3 weeks for a median duration of 15.1 months, in combination with gemcitabine and cisplatin, 3.4% tested positive for treatment-emergent ADA. Of the 190 evaluable patients in study POLARIS-02 with nasopharyngeal cancer who received LOQTORZI 3 mg/kg every 2 weeks for a median duration of 3.3 months, 3.7% of patients developed treatment-emergent ADA. Neutralizing antibodies have not been tested.

Due to the low incidence of ADA, the effect of these antibodies on the pharmacokinetics, pharmacodynamics, safety, or effectiveness of LOQTORZI is unknown.

13 NONCLINICAL TOXICOLOGY

13.1 Carcinogenesis, Mutagenesis, Impairment of Fertility

No studies have been performed to test the potential of toripalimab-tpzi for carcinogenicity or genotoxicity.

Fertility studies have not been conducted with toripalimab-tpzi. In 4-week and 26-week repeat-dose toxicology studies in sexually mature cynomolgus monkeys, there were no adverse or notable effects in the male and female reproductive organs.

13.2 Animal Toxicology and/or Pharmacology

In animal models, inhibition of PD-1/PD-L1 signaling increased the severity of some infections and enhanced inflammatory responses. Mycobacterium tuberculosis-infected PD-1 knockout mice exhibit markedly decreased survival compared with wild-type controls, which correlated with increased bacterial proliferation and inflammatory responses in these animals. PD-1 blockade using a primate anti-PD1 antibody was also shown to exacerbate M. tuberculosis infection in rhesus macaques. PD-1 and PD-L1 knockout mice and mice receiving PD-L1 blocking antibody have also shown decreased survival following infection with lymphocytic choriomeningitis virus.

14 CLINICAL STUDIES

14.1 First-line Treatment of Metastatic or Recurrent, Locally Advanced NPC with Cisplatin and Gemcitabine

The efficacy of LOQTORZI in combination with cisplatin and gemcitabine was investigated in JUPITER-02 (NCT03581786), a randomized, multicenter, single region, double-blind, placebo-controlled trial in 289 patients with metastatic or recurrent, locally advanced NPC who had not received previous systemic chemotherapy for recurrent or metastatic disease. Patients with recurrent NPC after treatment with curative intent were required to have an interval of at least 6 months between the last dose of radiotherapy or chemotherapy and recurrence. Patients with autoimmune disease, other than stable hypothyroidism or Type I diabetes, and patients who required systemic immunosuppression were ineligible.

Randomization was stratified according to Eastern Cooperative Oncology Group (ECOG) Performance Status (PS) (0 versus 1) and disease stage (recurrent versus metastatic). Patients were randomized (1:1) to receive one of the following treatments:

- LOQTORZI 240 mg intravenously every 3 weeks in combination with cisplatin 80 mg/m^2 on Day 1 every 3 weeks gemcitabine 1000 mg/m^2 on Days 1 and 8 for up to 6 cycles, followed by LOQTORZI 240 mg once every 3 weeks, or
- Placebo intravenously every 3 weeks in combination with cisplatin 80 mg/m^2 on Day 1 every 3 weeks and gemcitabine 1000 mg/m^2 on Days 1 and 8 for up to 6 cycles, followed by placebo once every 3 weeks.

Treatment with LOQTORZI or placebo continued until disease progression per RECIST v1.1, unacceptable toxicity, or a maximum of 2 years. Administration of LOQTORZI was permitted beyond radiographic progression if the patient was deriving benefit as assessed by the investigator. Tumor assessments were performed every 6 weeks for the first 12 months and every 9 weeks thereafter. The main efficacy outcome measure was Blinded Independent Review Committee (BIRC)-assessed progression-free survival (PFS) according to RECIST v1.1. Additional efficacy outcome measures include BIRC-assessed overall response rate (ORR) and overall survival (OS).

The study population characteristics were: median age of 48 years (range: 19 to 72), 4.8% age 65 or older, 83% male, 100% Asian, and 57% had ECOG PS of 0. Eighty-six percent of patients had metastatic disease at study entry. Histological subtypes of NPC included 98% non-keratinizing, 1% keratinizing squamous cell carcinoma, and 1% did not have the subtype identified.

Efficacy results of the pre-specified interim analysis of PFS and final analysis of OS are summarized in Table 7 and Figure 1 below. The trial demonstrated statistically significant improvements in BIRC-assessed PFS, ORR and OS for patients randomized to LOQTORZI in combination with cisplatin/gemcitabine compared to cisplatin and gemcitabine with placebo.

Table 7: Efficacy Results in JUPITER-02
Endpoints | LOQTORZI Cisplatin/Gemcitabine N =146 | Placebo Cisplatin/Gemcitabine N =143
BIRC-Assessed Progression-free Survival [PFS and ORR results are based on the pre-specified interim analysis with data cutoff of May 30, 2020.]
Number of Events, n (%) | 49 (34) | 79 (55)
Median, months (95% CI) | 11.7 (11.0, NE) | 8.0 (7.0, 9.5)
Hazard Ratio (95% CI) [Based on the stratified Cox proportional-hazards model using the stratification factors at randomization, ECOG performance status and disease stage.] | 0.52 (0.36, 0.74)
p-value [Two-sided p-value, based on the stratified log-rank test, as compared with an alpha boundary of 0.010.] | 0.0003
BIRC-Assessed Overall Response Rate
ORR, % (95% CI) | 77 (70, 84) | 66 (58, 74)
Complete Response Rate (%) | 19 | 11
Partial Response Rate (%) | 58 | 55
p-value [Two-sided p-value, based upon Cochran-Mantel-Haenszel test.] | 0.0353
BIRC-Assessed Duration of Response
Median, months (95% CI) | 10.0 (8.8, NE) | 5.7 (5.4, 6.8)
Overall Survival [OS results are based on the final analysis with a data cutoff of November 18, 2022.]
Number of Deaths, n (%) | 57 (39) | 76 (53)
Median, months (95% CI) | NR (38.7, NE) | 33.7 (27.0, 44.2)
Hazard Ratio (95% CI) | 0.63 (0.45, 0.89)
p-value [Two-sided p-value, based on the stratified log-rank test, as compared with an alpha boundary of 0.049995.] | 0.0083
BIRC=blinded independent review committee; CI= confidence interval; NR=Not Reached; NE=Not estimable.

Figure 1 Kaplan-Meier Curves of Overall Survival for JUPITER-02

14.2 Previously Treated Unresectable or Metastatic NPC

The efficacy of LOQTORZI was investigated in POLARIS-02 (NCT 02915432), an open-label, multicenter, multicohort trial conducted in a single country. The trial included a total of 172 patients with unresectable or metastatic NPC who had received prior platinum-based chemotherapy for treatment of recurrent or metastatic NPC or had disease progression within 6 months of completion of platinum-based chemotherapy administered as neoadjuvant, adjuvant, or definitive chemoradiation treatment for locally advanced disease. Key exclusion criteria included previous treatment with an anti-PD-(L)1 antibody; active autoimmune disease or other medical conditions requiring immunosuppressive therapy. Patients received LOQTORZI 3 mg/kg intravenously every 2 weeks until disease progression per RECIST v1.1 or unacceptable toxicity. Tumor response assessments were performed every 8 weeks for the first year and every 12 weeks thereafter. The major efficacy outcome measures were confirmed ORR and duration of response (DOR) as assessed by a Blinded Independent Review Committee (BIRC) using RECIST v1.1.

The median age was 45 years (range: 22 to 68), 4.1% age 65 or older, 83% male, 100% Asian, and Eastern Cooperative Oncology Group (ECOG) Performance Status (PS) of 0 (37%). Patients had received a median of 2 prior systemic therapies for recurrent/metastatic disease (range: 1-13). Ninety-five percent of patients had metastatic disease, 95% had non-keratinizing NPC, 2.9% had keratinizing squamous cell carcinoma and 1.7% did not have the subtype identified.

Efficacy results for POLARIS-02 are summarized in Table 8 below.

Table 8: Efficacy Results for POLARIS-02
Endpoint | LOQTORZI (N=172)
BIRC-Assessed Overall Response Rate [Confirmed overall response rate assessed by BIRC]
Overall Response Rate, % (95% CI) | 21 (15, 28)
Complete Response Rate, % | 2.3
Partial Response Rate, % | 19
BIRC-Assessed Duration of Response (DOR) | (N = 36)
Median, months (95% CI) | 14.9 (10.3, NE)
Patients with DOR≥ 6 months [Based on observed duration of response] , n (%) | 30 (83%)
Patients with DOR ≥ 12 months, n (%) | 14 (39%)
CI=confidence interval. n=number. NE = not estimable.
BIRC=blinded independent review committee

16 HOW SUPPLIED/STORAGE AND HANDLING

LOQTORZI (toripalimab-tpzi), injection is a clear to slightly opalescent, colorless to slightly yellow solution supplied in a carton containing one 240 mg/6 mL (40 mg/mL) single-dose vial (NDC 70114-340-01).

Store vials refrigerated at 2°C to 8°C (36°F to 46°F) in original carton to protect from light. Do not freeze. Do not shake.

17 PATIENT COUNSELING INFORMATION

Advise the patient to read the FDA-approved patient labeling (Medication Guide).

Immune-Mediated Adverse Reactions

Inform patients of the risk of immune-mediated adverse reactions that may be severe or fatal, may occur after discontinuation of treatment, and may require corticosteroid treatment and interruption or discontinuation of LOQTORZI. These reactions may include:

- Pneumonitis: Advise patients to contact their healthcare provider immediately for new or worsening cough, chest pain, or shortness of breath [see Warnings and Precautions (5.1)].
- Colitis: Advise patients to contact their healthcare provider immediately for diarrhea or severe abdominal pain [see Warnings and Precautions (5.1)].
- Hepatitis: Advise patients to contact their healthcare provider immediately for jaundice, severe nausea or vomiting, or easy bruising or bleeding [see Warnings and Precautions (5.1)].
- Endocrinopathies: Advise patients to contact their healthcare provider immediately for signs or symptoms of adrenal insufficiency, hypophysitis, hypothyroidism, hyperthyroidism, or Type 1 diabetes mellitus [see Warnings and Precautions (5.1)].
- Nephritis: Advise patients to contact their healthcare provider immediately for signs or symptoms of nephritis [see Warnings and Precautions (5.1)].
- Severe skin reactions: Advise patients to contact their healthcare provider immediately for any signs or symptoms of severe skin reactions, SJS or TEN [see Warnings and Precautions (5.1)].
- Other immune-mediated adverse reactions:
  - Advise patients that other immune-mediated adverse reactions can occur and may involve any organ system. Advise patients to contact their healthcare provider immediately for any new or worsening signs or symptoms [see Warnings and Precautions (5.1)].
  - Advise patients of the risk of solid organ transplant rejection and to contact their healthcare provider immediately for signs or symptoms of organ transplant rejection [see Warnings and Precautions (5.1)].

Infusion-Related Reactions

Advise patients to contact their healthcare provider immediately for signs or symptoms of infusion-related reactions [see Warnings and Precautions (5.2)].

Complications of Allogeneic HSCT

Advise patients of the risk of post-allogeneic hematopoietic stem cell transplantation complications [see Warnings and Precautions (5.3)].

Embryo-Fetal Toxicity

- Advise females of reproductive potential that LOQTORZI can cause harm to a fetus and to inform their healthcare provider of a known or suspected pregnancy [see Warnings and Precautions (5.4), Use in Specific Populations (8.1, 8.3)].
- Advise females of reproductive potential to use effective contraception during treatment with LOQTORZI and for 4 months after the last dose [see Warnings and Precautions (5.4), Use in Specific Populations (8.1, 8.3)].

Lactation

Advise women not to breastfeed during treatment with LOQTORZI and for 4 months after the last dose [see Use in Specific Populations (8.2)].

Laboratory Tests

Advise patients of the importance of keeping scheduled appointments for blood work or other laboratory tests [see Warnings and Precautions (5.1)].

Manufactured and Distributed by:

Coherus Oncology, Inc.
333 Twin Dolphin Drive, Suite 600
Redwood City, CA 94065, USA
U.S. License No. 2023

LOQTORZI® is a registered trademark of Coherus Oncology, Inc.
© 2024, Coherus Oncology, Inc.

PMD-0208, Rev: 03

Medication Guide
LOQTORZI (lok tor zee)
(toripalimab-tpzi)
injection

What is the most important information I should know about LOQTORZI?
LOQTORZI is a medicine that may treat nasopharyngeal cancer by working with your immune system. LOQTORZI can cause your immune system to attack normal organs and tissues in any area of your body and can affect the way they work. These problems can sometimes become severe or life-threatening and can lead to death. You can have more than one of these problems at the same time. These problems may happen anytime during treatment or even after treatment has ended.
Call or see your healthcare provider right away if you develop any new or worse signs or symptoms, including:
Lung problems

- cough

- shortness of breath

- chest pain

Intestinal problems

- diarrhea (loose stools) or more frequent bowel movements than usual
- stools that are black, tarry, sticky, or have blood or mucus
- severe stomach-area (abdomen) pain or tenderness

Liver problems

- yellowing of skin or the whites of your eyes
- severe nausea or vomiting
- pain on the right side of your stomach-area (abdomen)

- dark urine (tea colored)
- bleeding or bruising more easily than normal

Hormone gland problems

- headaches that will not go away or unusual headaches
- eye sensitivity to light
- eye problems
- rapid heartbeat
- increased sweating
- extreme tiredness
- weight gain or weight loss
- feeling more hungry or thirsty than usual

- urinating more often than usual
- hair loss
- feeling cold
- constipation
- your voice gets deeper
- dizziness or fainting
- change in mood or behavior, such as decreased sex drive, irritability, or forgetfulness

Kidney problems

- decrease in your amount of urine
- blood in your urine

- swelling of your ankles
- loss of appetite

Skin problems

- rash
- itching
- skin blistering or peeling

- painful sores or ulcers in your mouth or in your nose, throat, or genital area
- fever or flu-like symptoms
- swollen lymph nodes

Problems can also happen in other organs and tissues. These are not all of the signs and symptoms of immune system problems that can happen with LOQTORZI. Call or see your healthcare provider right away for any new or worsening signs or symptoms, which may include:

- chest pain, irregular heartbeat, shortness of breath, swelling of ankles
- confusion, sleepiness, memory problems, changes in mood or behavior, stiff neck, balance problems, tingling or numbness of the arms or legs
- double vision, blurry vision, sensitivity to light, eye pain, changes in eyesight
- persistent or severe muscle pain or weakness, muscle cramps
- low red blood cells, bruising

Infusion reactions that can sometimes be severe or life-threatening. Signs or symptoms of infusion reactions may include:

- chills or shaking
- itching or rash
- flushing
- shortness of breath or wheezing

- dizziness
- feeling like passing out
- fever
- back pain

Rejection of a transplanted organ. Your healthcare provider should tell you what signs and symptoms you should report and monitor, depending on the type of organ transplant that you have had.
Complications, including graft-versus-host disease (GVHD), in people who have received a bone marrow (stem cell) transplant that uses donor stem cells (allogeneic). These complications can be serious and can lead to death. These complications may happen if you underwent transplantation either before or after being treated with LOQTORZI. Your healthcare provider will monitor you for these complications.
Getting medical treatment right away may help keep these problems from becoming more serious.
Your healthcare provider will check you for these problems during treatment with LOQTORZI. Your healthcare provider may treat you with corticosteroid or hormone replacement medicines. Your healthcare provider may also need to delay or completely stop treatment with LOQTORZI if you have severe side effects.

What is LOQTORZI?
LOQTORZI is a prescription medicine used to treat adults with a kind of cancer called nasopharyngeal carcinoma (NPC).

- LOQTORZI may be used in combination with the chemotherapy medicines cisplatin and gemcitabine, as your first treatment when your NPC has spread to other parts of your body (metastatic) or has returned (recurrent) in nearby tissues (locally advanced).
- LOQTORZI may be used alone to treat your NPC when it:
  - has returned and cannot be removed with surgery or
  - has spread (metastatic), and
  - you received chemotherapy that contains platinum, and it did not work or is no longer working.

It is not known if LOQTORZI is safe and effective in children.

Before receiving LOQTORZI, tell your healthcare provider about all of your medical conditions, including if you:

- have immune system problems such as Crohn's disease, ulcerative colitis, or lupus
- have received an organ transplant
- have received or plan to receive a stem cell transplant that uses donor stem cells (allogeneic)
- have received radiation treatment to your chest area
- have had a condition that affects your nervous system, such as myasthenia gravis or Guillain-Barré syndrome
- are pregnant or plan to become pregnant. LOQTORZI can harm your unborn baby.
  Females who are able to become pregnant:
  - Your healthcare provider should do a pregnancy test before you start treatment with LOQTORZI.
  - You should use an effective method of birth control during your treatment and for 4 months after your last dose of LOQTORZI. Talk to your healthcare provider about birth control methods that you can use during this time.
  - Tell your healthcare provider right away if you think you may be pregnant or if you become pregnant during treatment with LOQTORZI.
- are breastfeeding or plan to breastfeed. It is not known if LOQTORZI passes into your breast milk. Do not breastfeed during treatment and for 4 months after the last dose of LOQTORZI.

Tell your healthcare provider about all the medicines you take, including prescription and over-the-counter medicines, vitamins, and herbal supplements.

How will I receive LOQTORZI?

- Your healthcare provider will give you LOQTORZI into your vein through an intravenous (IV) line over 30 or 60 minutes.
- LOQTORZI is usually given every two or three weeks as an intravenous (IV) infusion.
- Your healthcare provider will decide how many treatments you need.
- Your healthcare provider will test your blood to check you for certain side effects.
- If you miss any appointments, call your healthcare provider as soon as possible to reschedule.

What are the possible side effects of LOQTORZI?
LOQTORZI can cause serious side effects. See "What is the most important information I should know about LOQTORZI?"
Common side effects of LOQTORZI when used with cisplatin and gemcitabine include:

- nausea
- vomiting
- decreased appetite
- constipation
- low levels of thyroid hormone
- rash
- fever

- diarrhea
- burning or feeling of pins and needles in feet and toes
- cough
- muscle and bone pain
- upper respiratory infection
- sleep problems
- dizziness
- feeling generally unwell

Common side effects of LOQTORZI when used alone include:

- tiredness
- low levels of thyroid hormone
- muscle and bone pain

These are not all the possible side effects of LOQTORZI.
Call your doctor for medical advice about side effects. You may report side effects to FDA at 1-800-FDA-1088.

General information about the safe and effective use of LOQTORZI.
Medicines are sometimes prescribed for purposes other than those listed in a Medication Guide. You can ask your pharmacist or healthcare provider for information about LOQTORZI that is written for health professionals.

What are the ingredients in LOQTORZI?
Active ingredient: toripalimab-tpzi
Inactive ingredients: citric acid monohydrate, mannitol, polysorbate 80, sodium chloride, sodium citrate, and Water for Injection.
Manufactured and Distributed by: Coherus Oncology, Inc. 333 Twin Dolphin Drive, Suite 600 Redwood City, CA 94065, USA
US License No.: 2023
Copyright© 2023 Coherus Oncology, Inc.
All rights reserved.
For more information, call 1-800-483-3692 or go to www.coherus.com

This Medication Guide has been approved by the U.S. Food and Drug Administration.

Issued: 07/2025

PMD-0209, Rev. 01

PRINCIPAL DISPLAY PANEL - 240 mg/6 mL Vial Carton

NDC 70114-340-01
Rx Only

LOQTORZI™
(toripalimab-tpzi) injection

240 mg/6 mL (40 mg/mL)

For Intravenous Infusion After Dilution

ATTENTION PHARMACIST: Each patient is
required to receive the enclosed Medication Guide.

1 Single-dose vial. Discard unused portion.